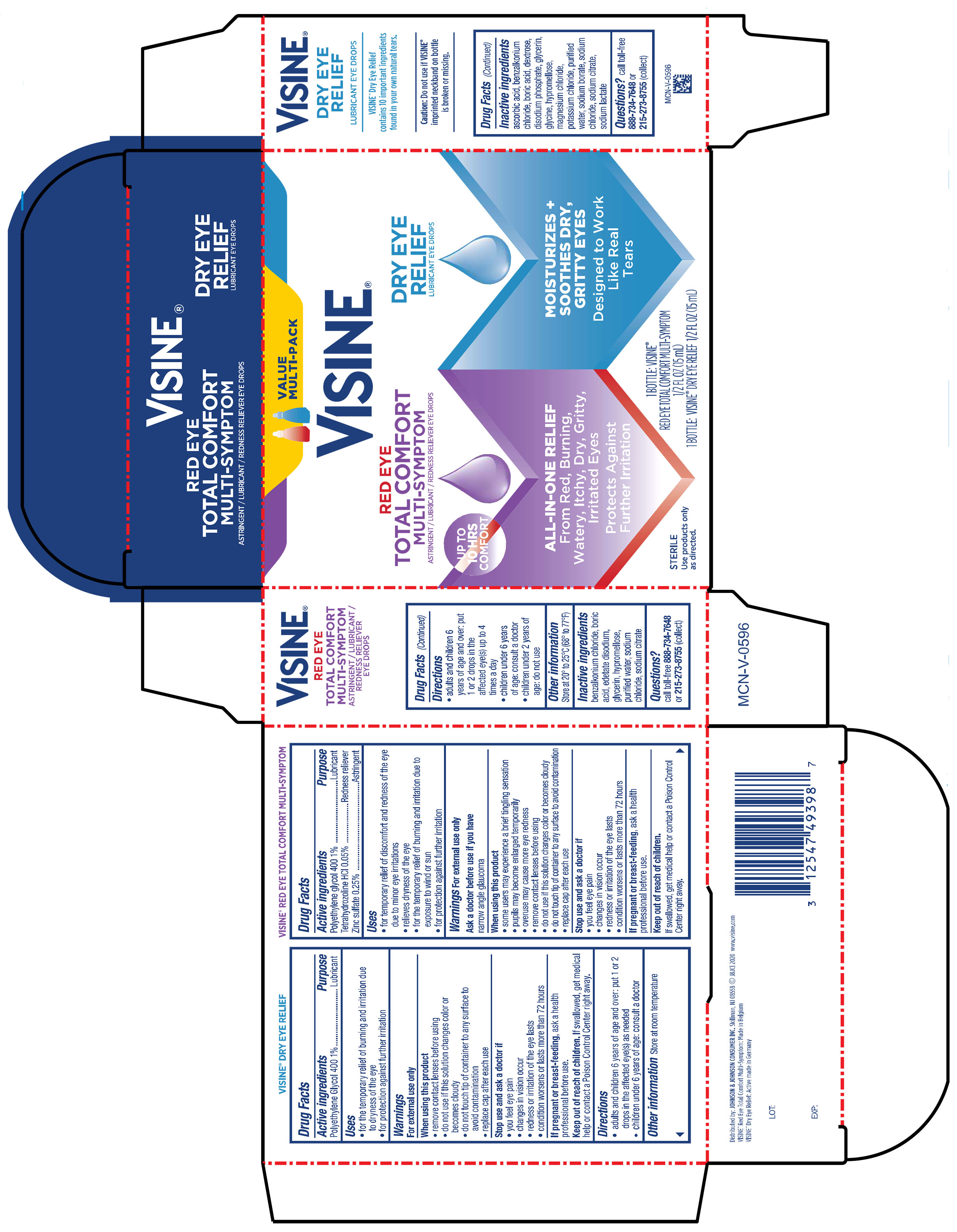 DRUG LABEL: Visine Red Eye Total Comfort and Tears Dry Eye Relief
NDC: 69968-0844 | Form: KIT | Route: OPHTHALMIC
Manufacturer: Kenvue Brands LLC
Category: otc | Type: HUMAN OTC DRUG LABEL
Date: 20241114

ACTIVE INGREDIENTS: TETRAHYDROZOLINE HYDROCHLORIDE 0.5 mg/1 mL; ZINC SULFATE, UNSPECIFIED FORM 2.5 mg/1 mL; POLYETHYLENE GLYCOL 400 10 mg/1 mL; POLYETHYLENE GLYCOL 400 10 mg/1 mL
INACTIVE INGREDIENTS: BORIC ACID; SODIUM CITRATE; EDETATE DISODIUM; HYPROMELLOSES; WATER; GLYCERIN; SODIUM CHLORIDE; BENZALKONIUM CHLORIDE; GLYCINE; BENZALKONIUM CHLORIDE; DEXTROSE; SODIUM CHLORIDE; SODIUM PHOSPHATE, DIBASIC, ANHYDROUS; POTASSIUM CHLORIDE; GLYCERIN; WATER; BORIC ACID; MAGNESIUM CHLORIDE; SODIUM LACTATE; ASCORBIC ACID; SODIUM CITRATE; HYPROMELLOSES; SODIUM BORATE

Visine Red Eye Total Comfort and Tears Dry Eye Relief

VISINE® Red Eye Total Comfort Multi-Symptom

Drug Facts

Active ingredient

Polyethylene glycol 400 1%

Tetrahydrozoline HCl 0.05%

Zinc sulfate 0.25%

Purpose

Lubricant

Redness reliever

Astringent

Uses

- for the temporary relief of discomfort and redness of the eye due to minor eye irritations
- relieves dryness of the eye
- for the temporary relief of burning and irritation due to exposure to wind or sun
- for protection against further irritation

Warnings

For external use only

Ask a doctor before use if you have narrow angle glaucoma.

When using this product

• some users may experience a brief tingling sensation
• pupils may become enlarged temporarily

• overuse may cause more eye redness

• remove contact lenses before using

• do not use if this solution changes color or becomes cloudy

• do not touch tip of container to any surface to avoid contamination

• replace cap after each use

Stop use and ask a doctor if

• you feel eye pain

• changes in vision occur

• redness or irritation of the eye lasts

• condition worsens or lasts more than 72 hours

PREGNANCY OR BREAST FEEDING

If pregnant or breast-feeding, ask a health professional before use.

Keep out of reach of children. If swallowed, get medical help or contact a Poison Control Center right away.

Directions

• adults and children 6 years of age and over: put 1 or 2 drops in the affected eye(s) up to 4 times a day

• children under 6 years of age: consult a doctor

• children under 2 years of age: do not use

Other information

Store at 20° to 25°C (68° to 77°F)

Inactive ingredients

benzalkonium chloride, boric acid, edetate disodium, glycerin, hypromellose, purified water, sodium chloride, sodium citrate

Questions?

call toll-free 888-734-7648 or 215-273-8755 (collect)

VISINE® Dry Eye Relief

Drug Facts

Active ingredient

Polyethylene glycol 400 1%

Purpose

Lubricant

Uses

- for the temporary relief of burning and irritation due to dryness of the eye
- for protection against further irritation

Warnings

For external use only

When using this product

• remove contact lenses before using

• do not use if this solution changes color or becomes cloudy

• do not touch tip of container to any surface to avoid contamination

• replace cap after each use

Stop use and ask a doctor if

• you feel eye pain

• changes in vision occur

• redness or irritation of the eye lasts

• condition worsens or lasts more than 72 hours

PREGNANCY OR BREAST FEEDING

If pregnant or breast-feeding, ask a health professional before use.

Keep out of reach of children. If swallowed, get medical help or contact a Poison Control Center right away.

Directions

• adults and children 6 years of age and over: put 1 or 2 drops in the affected eye(s) as needed

• children under 6 years of age: consult a doctor

Other information

Store at room temperature

Inactive ingredients

ascorbic acid, benzalkonium chloride, boric acid, dextrose, disodium phosphate, glycerin, glycine, hypromellose, magnesium chloride, potassium chloride, purified water, sodium borate, sodium chloride, sodium citrate, sodium lactate

Questions?

call toll-free 888-734-7648 or 215-273-8755 (collect)

Distributed by:
JOHNSON & JOHNSON CONSUMER INC.
Skillman, NJ 08558

PRINCIPAL DISPLAY PANEL - Kit Package

VALUE

MULTI-PACK

VISINE®

RED EYE

TOTAL COMFORT

MULTI-SYMPTOM

ASTRINGENT / LUBRICANT / REDNESS RELIEVER EYE DROPS

UP TO

10 HRS

COMFORT

ALL-IN ONE RELIEF

From Red, Burning,

Watery, Itchy, Dry, Gritty,

Irritated Eyes

Protects Against

Further Irritation

STERILE

Use products only

as directed.

DRY EYE

RELIEF

LUBRICANT EYE DROPS

MOISTURIZES +

SOOTHES DRY,

GRITTY EYES

Designed to Work

Like Real

Tears

1 BOTTLE: VISINE®

RED EYE TOTAL COMFORT MULTI-SYMPTOM

½ FL OZ (15 mL)

1 BOTTLE: VISINE® DRY EYE RELIEF ½ FL OZ (15 mL)